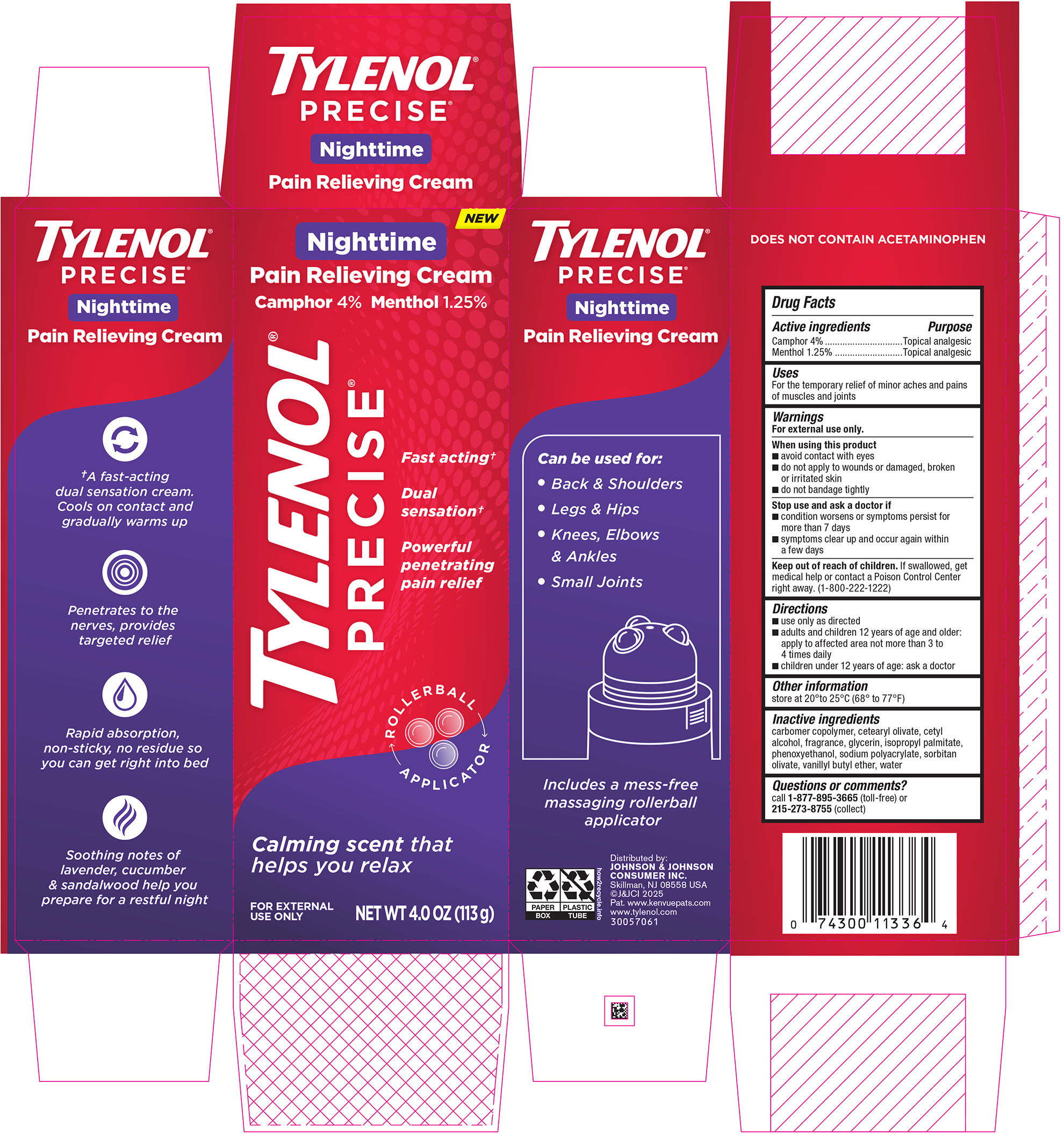 DRUG LABEL: Tylenol Precise Nighttime Pain Relieving
NDC: 69968-0905 | Form: CREAM
Manufacturer: Kenvue Brands LLC
Category: otc | Type: HUMAN OTC DRUG LABEL
Date: 20250225

ACTIVE INGREDIENTS: CAMPHOR (SYNTHETIC) 40 mg/1 g; MENTHOL 12.5 mg/1 g
INACTIVE INGREDIENTS: CARBOMER INTERPOLYMER TYPE A (55000 CPS); WATER; GLYCERIN; PHENOXYETHANOL; SORBITAN OLIVATE; VANILLYL BUTYL ETHER; CETEARYL OLIVATE; CETYL ALCOHOL; ISOPROPYL PALMITATE

Tylenol Precise Nighttime Pain Relieving Cream

Drug Facts

Active ingredients Purpose

Camphor 4%............................................................................................. Topical analgesic

Menthol 1.25% ..........................................................................................Topical analgesic

Uses

For the temporary relief of minor aches and pains of muscles and joints

Warnings

For external use only.

When using this product

- avoid contact with eyes
- do not apply to wounds or damaged, broken or irritated skin
- do not bandage tightly

Stop use and ask a doctor if

- condition worsens or symptoms persist for more than 7 days
- Symptoms clear up and occur again within a few days

Keep out of reach of children. If swallowed, get medical help or contact a Poison Control Center right away. (1-800-222-1222)

Directions

- use only as directed
- adults and children 12 years of age and older: apply to affected area not more than 3 to 4 times daily
- Children under 12 years of age: ask a doctor

Other Information

- store at 20˚ to 25 ˚C (68 ˚ to 77 ˚F)

Inactive Ingredients

carbomer copolymer, cetearyl olivate, cetyl alcohol, fragrance, glycerin, isopropyl palmitate, phenoxyethanol, sodium polyacrylate, sorbitan olivate, vanillyl butyl ether, water

Questions or comments?

call 1-877-895-3665 (toll-free) or 215-273-8755 (collect)

Distributed by:
JOHNSON & JOHNSON CONSUMER INC.
Skillman, NJ 08558 USA

PRINCIPAL DISPLAY PANEL - 113 g Tube Carton

NEW

Nighttime

Pain Relieving Cream

Camphor 4% Menthol 1.25%

TYLENOL®

PRECISE®

Fast acting†

Dual

sensation†

Powerful

penetrating

pain relief

ROLLERBALL

APPLICATOR

Calming scent that

helps you relax

FOR EXTERNAL

USE ONLY

NET WT 4.0 OZ (113 g)